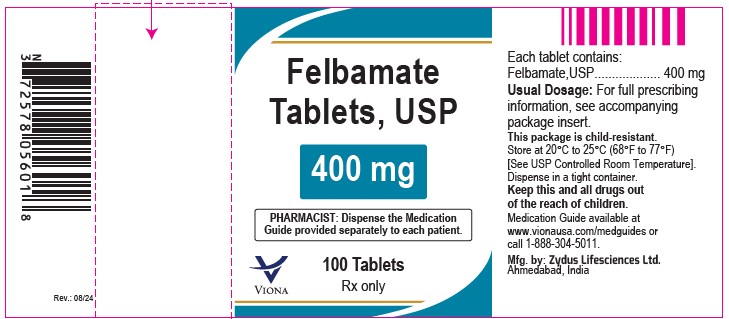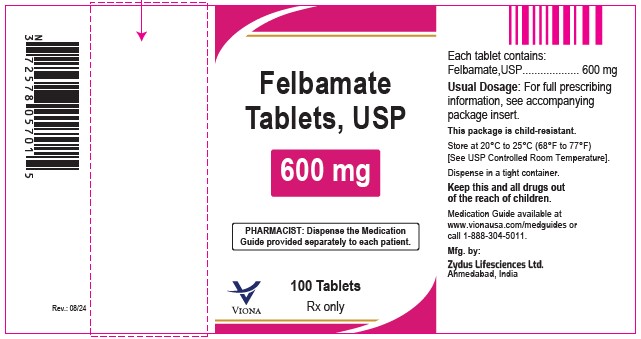 DRUG LABEL: Felbamate
NDC: 70771-1077 | Form: TABLET
Manufacturer: Zydus Lifesciences Limited
Category: prescription | Type: HUMAN PRESCRIPTION DRUG LABEL
Date: 20240816

ACTIVE INGREDIENTS: FELBAMATE 400 mg/1 1
INACTIVE INGREDIENTS: ALUMINUM OXIDE; CELLULOSE, MICROCRYSTALLINE; FD&C RED NO. 40; FERRIC OXIDE YELLOW; LACTOSE MONOHYDRATE; MAGNESIUM STEARATE; POVIDONE K30; SILICON DIOXIDE; SODIUM STARCH GLYCOLATE TYPE A POTATO; STARCH, CORN

Felbamate Tablets, USP

PACKAGE LABEL.PRINCIPAL DISPLAY PANEL

NDC 70771-1077-1

Felbamate tablets USP, 400 mg

100 Tablets

Rx only

NDC 70771-1078-1

Felbamate tablets USP, 600 mg

100 Tablets

Rx only